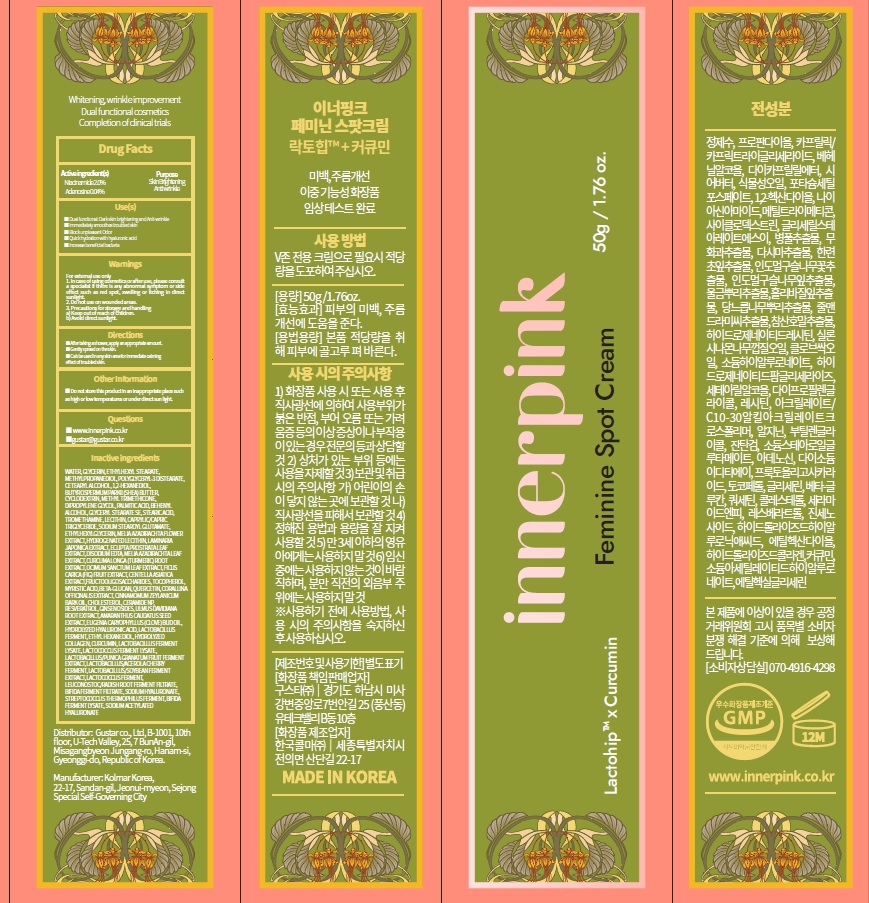 DRUG LABEL: innerpink Feminine Spot
NDC: 73819-0015 | Form: CREAM
Manufacturer: GuStar Co., Ltd.
Category: otc | Type: HUMAN OTC DRUG LABEL
Date: 20230419

ACTIVE INGREDIENTS: Niacinamide 2.0 g/100 g; Adenosine 0.04 g/100 g
INACTIVE INGREDIENTS: WATER; GLYCERIN; ETHYLHEXYL STEARATE

Drug Facts

Active ingredient(s)

Niacinamide 2.0%
Adenosine 0.04%

INACTIVE INGREDIENTS

WATER, GLYCERIN, ETHYLHEXYL STEARATE, METHYLPROPANEDIOL, POLYGLYCERYL-3 DISTEARATE, CETEARYL ALCOHOL, 1,2-HEXANEDIOL, BUTYROSPERMUM PARKII (SHEA) BUTTER, CYCLODEXTRIN, METHYL TRIMETHICONE, DIPROPYLENE GLYCOL, PALMITIC ACID, BEHENYL ALCOHOL, GLYCERYL STEARATE SE, STEARIC ACID, TROMETHAMINE, LECITHIN, CAPRYLIC/CAPRIC TRIGLYCERIDE, SODIUM STEAROYL GLUTAMATE, ETHYLHEXYLGLYCERIN, MELIA AZADIRACHTA FLOWER EXTRACT, HYDROGENATED LECITHIN, LAMINARIA JAPONICA EXTRACT, ECLIPTA PROSTRATA LEAF EXTRACT, DISODIUM EDTA, MELIA AZADIRACHTA LEAF EXTRACT, CURCUMA LONGA (TURMERIC) ROOT EXTRACT, OCIMUM SANCTUM LEAF EXTRACT, FICUS CARICA (FIG) FRUIT EXTRACT, CENTELLA ASIATICA EXTRACT,FRUCTOOLIGOSACCHARIDES, TOCOPHEROL, MYRISTIC ACID, BETA-GLUCAN, QUERCETIN, CORALLINA OFFICINALIS EXTRACT, CINNAMOMUM ZEYLANICUM BARK OIL, CHOLESTEROL, CERAMIDE NP, RESVERATROL, GINSENOSIDES, ULMUS DAVIDIANA ROOT EXTRACT, AMARANTHUS CAUDATUS SEED EXTRACT, EUGENIA CARYOPHYLLUS (CLOVE) BUD OIL, HYDROLYZED HYALURONIC ACID, LACTOBACILLUS FERMENT, ETHYL HEXANEDIOL, HYDROLYZED COLLAGEN, CURCUMIN, LACTOBACILLUS FERMENT LYSATE, LACTOCOCCUS FERMENT LYSATE, LACTOBACILLUS/PUNICA GRANATUM FRUIT FERMENT EXTRACT, LACTOBACILLUS/ACEROLA CHERRY FERMENT, LACTOBACILLUS/SOYBEAN FERMENT EXTRACT, LACTOCOCCUS FERMENT, LEUCONOSTOC/RADISH ROOT FERMENT FILTRATE, BIFIDA FERMENT FILTRATE, SODIUM HYALURONATE, STREPTOCOCCUS THERMOPHILUS FERMENT, BIFIDA FERMENT LYSATE, SODIUM ACETYLATED HYALURONATE

PURPOSE

Skin Brightening
Anti wrinkle

WARNINGS

For external use only
1. In case of using cosmetics or after use, please consult a specialist if there is any abnormal symptom or side effect such as red spot, swelling or itching in direct sunlight.
2. Do not use on wounded areas.
3. Precautions for storage and handling
a) Keep out of reach of children.
b) Avoid direct sunlight.

KEEP OUT OF REACH OF CHILDREN

Use(s)

■ Dual functional: Dark skin brightening and Anti-wrinkle
■ Immediately smoothes troubled skin
■ Block unpleasant Odor
■ Quick hydration with hyaluronic acid
■ Increase beneficial bacteria

Directions

■ After taking a shower, apply an appropriate amount.
■ Gently spread on the skin.
■ Can be used in any skin area for immediate calming effect of troubled skin.

Other Information

■ Do not store this product in an inappropriate place such as high or low temperatures or under direct sun light.

Questions

■ www.innerpink.co.kr